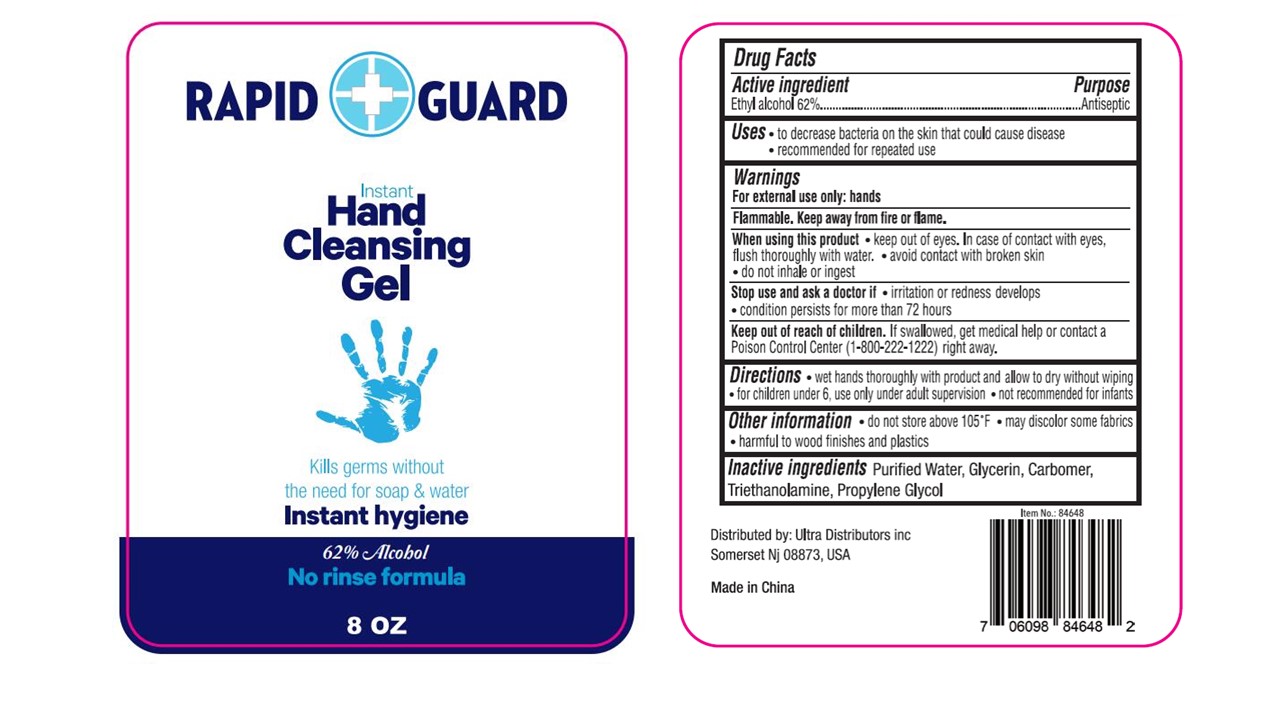 DRUG LABEL: 62% alcohol hand sanitizer
NDC: 78495-015 | Form: GEL
Manufacturer: Ultra Distributors Inc
Category: otc | Type: HUMAN OTC DRUG LABEL
Date: 20211223

ACTIVE INGREDIENTS: ALCOHOL 146.32 mL/236 mL
INACTIVE INGREDIENTS: PROPYLENE GLYCOL; GLYCERIN; TROLAMINE; CARBOMER HOMOPOLYMER, UNSPECIFIED TYPE; WATER

PURPOSE

Disinfection
Sterilization
No Rinseing

ACTIVE INGREDIENT

Alcohol62%

INDICATIONS AND USAGE

Directions: Pour a sufficient amount of the liquid into the palm of your dry hands. Rub thoroughly all over hands briskly until dry. Repeat if necessary. Use without water. Use only under adult supervision.

WARNINGS

Warnings: Highly flammable liquid and vapour. Causes serious eye iritation. May cause skin iritation. Keep away from heat, sparks, hot surfaces, fire, open flame and sources of ignition. No smoking. Keep at room temperature. Store in a well-ventilated, cool and dry place, away from direct sunlight. Do not store above 40 °C

For external use only.

Avoid contact with eyes. If in eyes, rinse immediately with clean water for several minutes. Remove contact lenses, if present and easy to do. Continue rinsing. Do not swallow. If swallowed, rinse mouth and seek medical advice immediately and show this label. Do not induce vomiting. Do not use on damage, inflamed or broken skin. If iritation or redness develops, discontinue use.

Keep out of the reach of babies, children & animals.

DOSAGE AND ADMINISTRATION

236ml store in ventilated shade and Do not store above 40 °C

INACTIVE INGREDIENT

Alcohol, water/eau/aqua, carbomer，triethanolamine, propylene glycol, glycerin